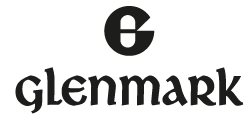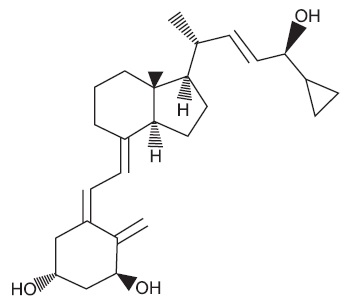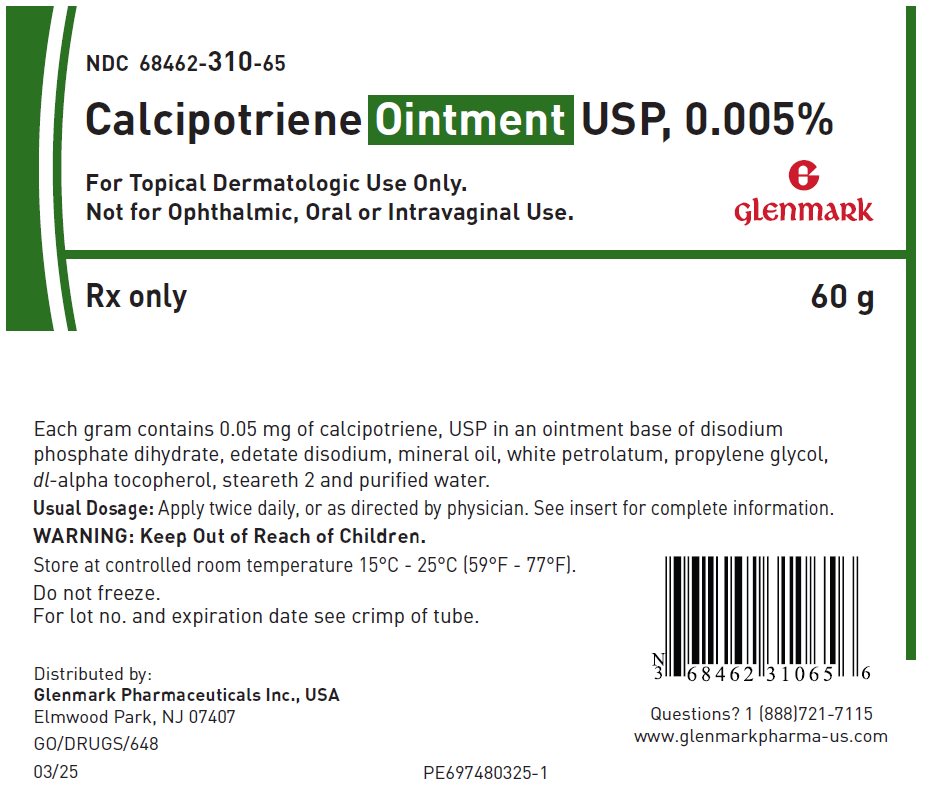 DRUG LABEL: Calcipotriene
NDC: 68462-310 | Form: OINTMENT
Manufacturer: Glenmark Pharmaceuticals Inc., USA
Category: prescription | Type: HUMAN PRESCRIPTION DRUG LABEL
Date: 20260123

ACTIVE INGREDIENTS: CALCIPOTRIENE 50 ug/1 g
INACTIVE INGREDIENTS: SODIUM PHOSPHATE, DIBASIC, DIHYDRATE; EDETATE DISODIUM; MINERAL OIL; PETROLATUM; PROPYLENE GLYCOL; .ALPHA.-TOCOPHEROL; WATER; STEARETH-2

Calcipotriene Ointment USP, 0.005%

Rx Only

FOR TOPICAL DERMATOLOGIC USE ONLY.

Not for Ophthalmic, Oral or Intravaginal Use.

DESCRIPTION

Calcipotriene Ointment USP, 0.005% contains the compound calcipotriene, USP a synthetic vitamin D3 derivative for topical dermatological use.

Chemically, Calcipotriene, USP is 24-cyclopropyl-(1α,3β,5Z,7E,22E,24S)-9,10-Secochola-5,7,10(19),22-tetraene-1,3,24-trioI; with the empirical formula C27H40O3, a molecular weight of 412.62, and the following structural formula:

Calcipotriene, USP is a white or almost white crystalline powder. Calcipotriene Ointment USP, 0.005% contains calcipotriene, USP 50 mcg/g in an ointment base of disodium phosphate dihydrate, edetate disodium, mineral oil, white petrolatum, propylene glycol, dl-alpha-tocopherol, steareth-2 and purified water.

CLINICAL PHARMACOLOGY

In humans, the natural supply of vitamin D depends mainly on exposure to the ultraviolet rays of the sun for conversion of 7-dehydrocholesterol to vitamin D3 (cholecalciferol) in the skin. Calcipotriene is a synthetic analog of vitamin D3.

Clinical studies with radiolabelled calcipotriene ointment, USP indicate that approximately 6% (± 3%, SD) of the applied dose of calcipotriene is absorbed systemically when the ointment is applied topically to psoriasis plaques or 5% (± 2.6%, SD) when applied to normal skin, and much of the absorbed active is converted to inactive metabolites within 24 hours of application.

Vitamin D and its metabolites are transported in the blood, bound to specific plasma proteins. The active form of the vitamin, 1,25-dihydroxy vitamin D3 (calcitriol), is known to be recycled via the liver and excreted in the bile. Calcipotriene metabolism following systemic uptake is rapid, and occurs via a similar pathway to the natural hormone. The primary metabolites are much less potent than the parent compound.

There is evidence that maternal 1,25-dihydroxy vitamin D3 (calcitriol) may enter the fetal circulation, but it is not known whether it is excreted in human milk. The systemic disposition of calcipotriene is expected to be similar to that of the naturally occurring vitamin.

CLINICAL STUDIES

Adequate and well-controlled trials of patients treated with calcipotriene ointment USP, 0.005% have demonstrated improvement usually beginning after 2 weeks of therapy. This improvement continued in patients using calcipotriene once daily and twice daily. After 8 weeks of once daily calcipotriene, 56.7% of patients showed at least marked improvements (6.4% showed complete clearing). After 8 weeks of twice daily calcipotriene, 70% of patients showed at least marked improvement (11.3% showed complete clearing).

Subtracting percentages of patients using placebo (vehicle only) from percentages of patients using calcipotriene who had at least marked improvements after 8 weeks yields 39.9% for once daily and 49.6% for twice daily. This adjustment for placebo effect indicates that what might appear to be differences between once and twice daily use may reflect differences in the studies independent from the frequency of dosing. Although there was a numerical difference in comparison across studies, twice daily dosing has not been shown to be superior in efficacy to once daily dosing.

Over 400 patients have been treated in open label clinical studies of calcipotriene for periods of up to one year. In half of these studies, patients who previously had not responded well to calcipotriene were excluded. The adverse reaction in these extended studies included skin irritation in approximately 25% of patients and worsening of psoriasis in approximately 10% of patients. In one of these open label studies, half of the patients no longer required calcipotriene by 16 weeks of treatment, because of satisfactory therapeutic results.

INDICATIONS AND USAGE

Calcipotriene ointment USP, 0.005%, is indicated for the treatment of plaque psoriasis in adults. The safety and effectiveness of topical calcipotriene in dermatoses other than psoriasis have not been established.

CONTRAINDICATIONS

Calcipotriene is contraindicated in those patients with a history of hypersensitivity to any of the components of the preparation. It should not be used by patients with demonstrated hypercalcemia or evidence of vitamin D toxicity. Calcipotriene should not be used on the face.

WARNINGS

Contact dermatitis, including allergic contact dermatitis, has been observed with the use of calcipotriene.

PRECAUTIONS

General

Use of calcipotriene may cause irritation of lesions and surrounding uninvolved skin. If irritation develops, calcipotriene should be discontinued.

For external use only. Keep out of the reach of children. Always wash hands thoroughly after use.

Reversible elevation of serum calcium has occurred with use of calcipotriene. If elevation in serum calcium outside the normal range should occur, discontinue treatment until normal calcium levels are restored.

Information for Patients

Patients using calcipotriene should receive the following information and instructions:

1. This medication is to be used as directed by the physician. It is for external use only. Avoid contact with the face or eyes. As with any topical medication, patients should wash their hands after application.
2. This medication should not be used for any disorder other than that for which it was prescribed.
3. Patients should report to their physician any signs of local adverse reactions.
4. Patients that apply calcipotriene to exposed portions of the body should avoid excessive exposure to either natural or artificial sunlight. (including tanning booths, sun lamps, etc.)

Carcinogenesis, Mutagenesis, Impairment of Fertility

When calcipotriene was applied topically to mice for up to 24 months at dosages of 3, 10 and 30 mcg/kg/day (corresponding to 9, 30 and 90 mcg/m^2/day), no significant changes in tumor incidence were observed when compared to control. In a study in which albino hairless mice were exposed to both UVR and topically applied calcipotriene, a reduction in the time required for UVR to induce the formation of skin tumors was observed (statistically significant in males only), suggesting that calcipotriene may enhance the effect of UVR to induce skin tumors. Patients that apply calcipotriene to exposed portions of the body should avoid excessive exposure to either natural or artificial sunlight (including tanning booths, sun lamps, etc.). Physicians may wish to avoid use of phototherapy in patients that use calcipotriene ointment USP, 0.005%.

Calcipotriene did not elicit any mutagenic effects in an Ames mutagenicity assay, a mouse lymphoma TK locus assay, a human lymphocyte chromosome aberration assay, or in a micronucleus assay conducted in mice.

Studies in rats at doses up to 54 mcg/kg/day (324 mcg/m^2/day) of calcipotriene indicated no impairment of fertility or general reproductive performance.

Pregnancy

Teratogenic Effects

Studies of teratogenicity were done by the oral route where bioavailability is expected to be approximately 40 to 60% of the administered dose. In rabbits, increased maternal and fetal toxicity were noted at a dosage 12 mcg/kg/day (132 mcg/m^2/day); a dosage of 36 mcg/kg/day (396 mcg/m^2/day) resulted in a significant increase in the incidence of incomplete ossification of the pubic bones and forelimb phalanges of fetuses. In a rat study, a dosage of 54 mcg/kg/day (318 mcg/m^2/day) resulted in a significantly increased incidence of skeletal abnormalities (enlarged fontanelles and extra ribs). The enlarged fontanelles are most likely due to calcipotriene's effect upon calcium metabolism. The estimated maternal and fetal no-effect exposure levels in the rat (43.2 mcg/m^2/day) and rabbit (17.6 mcg/m^2/day) studies are approximately equal to the expected human systemic exposure level (18.5 mcg/m^2/day) from dermal application. There are no adequate and well-controlled studies in pregnant women. Therefore, calcipotriene ointment should be used during pregnancy only if the potential benefit justifies the potential risk to the fetus.

Nursing Mothers

It is not known whether calcipotriene is excreted in human milk. Because many drugs are excreted in human milk, caution should be exercised when calcipotriene ointment, 0.005% is administered to a nursing woman.

Pediatric Use

Safety and effectiveness of calcipotriene in pediatric patients have not been established. Because of a higher ratio of skin surface area to body mass, pediatric patients are at greater risk than adults of systemic adverse effects when they are treated with topical medication.

Geriatric Use

Of the total number of patients in clinical studies of calcipotriene ointment, USP approximately 12% were 65 or older, while approximately 4% were 75 and over. The results of an analysis of severity of skin-related adverse events showed a statistically significant difference for subjects over 65 years (more severe) compared to those under 65 years (less severe).

ADVERSE REACTIONS

Clinical Trials Experience

In controlled clinical trials, the most frequent adverse reactions reported for calcipotriene were burning, itching and skin irritation, which occurred in approximately 10 to 15% of patients. Erythema, dry skin, peeling, rash, dermatitis, worsening of psoriasis including development of facial/scalp psoriasis were reported in 1 to 10% of patients. Other experiences reported in less than 1% of patients included skin atrophy, hyperpigmentation, hypercalcemia, and folliculitis. Once daily dosing has not been shown to be superior in safety to twice daily dosing.

Postmarketing Experience

The following adverse reactions have been identified during post approval use of Dovonex Ointment. Because these reactions are reported voluntarily from a population of uncertain size, it is not always possible to reliably estimate their frequency or establish a causal relationship to drug exposure.

Renal and urinary disorders: hypercalciuria

Skin and subcutaneous tissue disorders: application site edema, application site pain, contact dermatitis (including allergic contact dermatitis), depigmentation, hypopigmentation, photosensitivity, rash (including erythematous, maculo-papular, and pustular), and urticaria.

OVERDOSAGE

Topically applied calcipotriene can be absorbed in sufficient amounts to produce systemic effects. Elevated serum calcium has been observed with excessive use of calcipotriene ointment USP, 0.005%.

DOSAGE AND ADMINISTRATION

Apply a thin layer of calcipotriene ointment USP, 0.005% once or twice daily and rub in gently and completely.

HOW SUPPLIED

Calcipotriene Ointment USP, 0.005% is available in:

60 gram aluminum tube NDC (68462-310-65)

120 gram aluminum tube NDC (68462-310-66)

STORAGE

Store at controlled room temperature 15°C to 25°C (59°F to 77°F). Do not freeze.

Distributed by:

Glenmark Pharmaceuticals Inc., USA
Elmwood Park, NJ 07407

Questions? 1 (888)721-7115
www.glenmarkpharma-us.com

November 2025